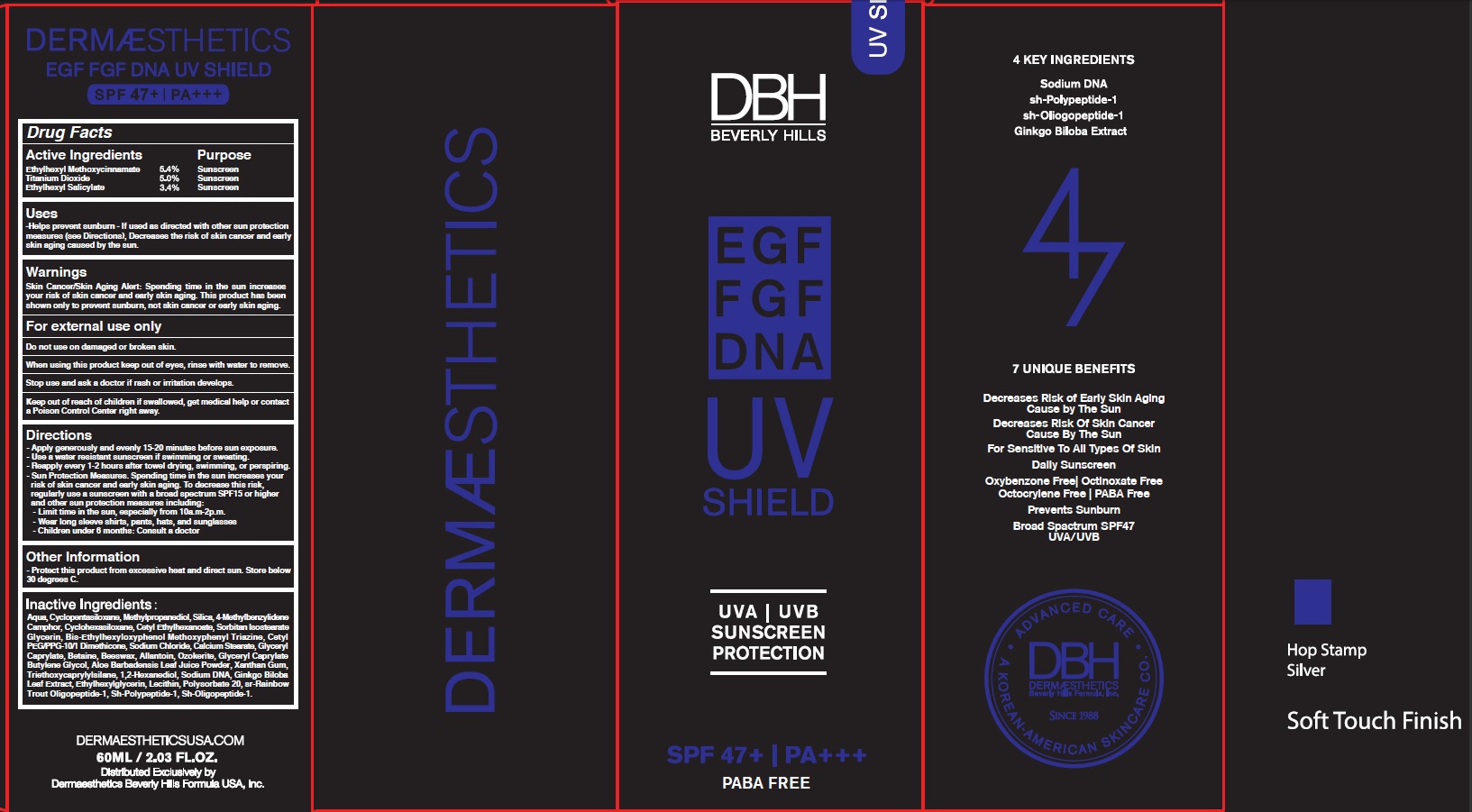 DRUG LABEL: EGF FGF DNA UV SHIELD
NDC: 58831-1100 | Form: CREAM
Manufacturer: Dermaesthetics Inc.
Category: otc | Type: HUMAN OTC DRUG LABEL
Date: 20241204

ACTIVE INGREDIENTS: OCTINOXATE 3.24 g/60 mL; TITANIUM DIOXIDE 3 g/60 mL; OCTISALATE 2.04 g/60 mL
INACTIVE INGREDIENTS: WATER; CYCLOMETHICONE 5

ACTIVE INGREDIENTS

Ethylhexyl Methoxycinnamate 5.40%
Titanium Dioxide 5.00%
Ethylhexyl Salicylate 3.40%

INACTIVE INGREDIENTS

Aqua, Cyclopentasiloxane, Silica, 4-Methylbenzylidene Camphor, Cyclohexasiloxane, Cetyl Ethylhexanoate, Sorbitan Isostearate, Glycerin,
Bis-Ethylhexyloxyphenol Methoxyphenyl Triazine, Cetyl PEG/PPG-10/1 Dimethicone, Sodium Chloride, Calcium Stearate, Glyceryl Caprylate, Betaine, Beeswax, Allantoin, Ozokerite, Glyceryl Caprylate, Butylene Glycol, Aloe Barbadensis Leaf Juice Powder, Xanthan Gum, Triethoxycaprylylsilane, 1,2-Hexanediol, Sodium DNA, Ginkgo Biloba Leaf Extract, Ethylhexylglycerin, Lecithin, Polysorbate 20, sr-Rainbow Trout Oligopeptide-1 sh-Oligopeptide-1, sh-Oligopeptide-1.

PURPOSE

Sunscreen

WARNINGS

Skin Cancer/Skin Aging Alert: Spending time in the sun increases your risk of skin cancer and early skin aging. This product has been shown only to prevent sunburn, not skin cancer or early skin aging.

■ For external use only

■ Do not use on damaged or broken skin.
■ When using this product keep out of eyes, rinse with water to remove.
■ Stop use and ask a doctor if rash or irritation develops.
■ Keep out of reach of children if swallowed, get medical help or contact a Poison Control Center right away.

■ Keep out of reach of children if swallowed, get medical help or contact a Poison Control Center right away.

Uses:
■ Helps prevent sun burn
■ If used as directed with other sun protection measures (see Directions), decreases the risk of skin cancer and early skin aging caused by the sun.

Directions:
■ Apply generously and evenly 15-20 minutes before sun exposure.
■ Use a water resistant sunscreen if swimming or sweating.
■ Reapply every 1-2 hours after towel drying, swimming, or perspiring.
■ Sun Protection Measures. Spending time in the sun increases your risk of skin cancer and early skin aging. To decrease this risk, regularly use a sunscreen with a broad spectrum SPF 15 or higher and other sun protection measures including:
- Limit time in the sun, especially from 10a.m-2p.m.
- Wear long sleeve shirts, pants, hats, and sunglasses.
- Children under 6 months: Consult a doctor.

Other Information

■ Protect this product from excessive heat and direct sun.